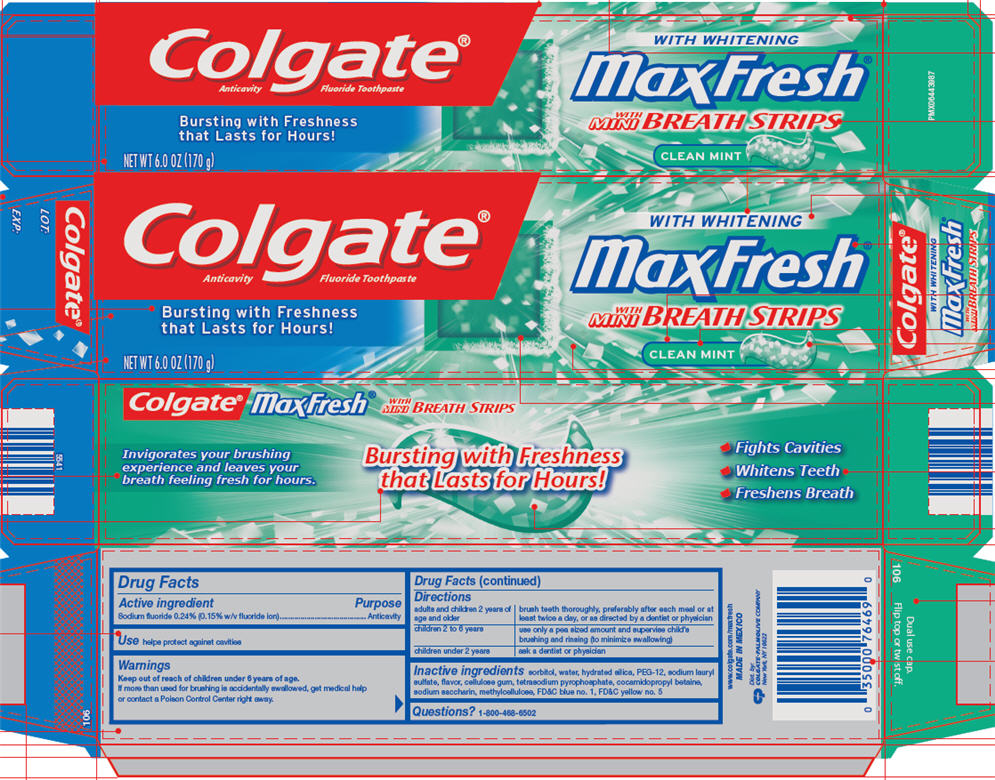 DRUG LABEL: Colgate Max Fresh Clean Mint
NDC: 35000-902 | Form: GEL, DENTIFRICE
Manufacturer: Colgate-Palmolive Company
Category: otc | Type: HUMAN OTC DRUG LABEL
Date: 20191127

ACTIVE INGREDIENTS: SODIUM FLUORIDE 2.4 mg/1 g
INACTIVE INGREDIENTS: SORBITOL 564.38 mg/1 g; WATER; HYDRATED SILICA; POLYETHYLENE GLYCOL 600; SODIUM LAURYL SULFATE; CARBOXYMETHYLCELLULOSE SODIUM, UNSPECIFIED; SODIUM PYROPHOSPHATE; COCAMIDOPROPYL BETAINE; SACCHARIN SODIUM; POWDERED CELLULOSE; FD&C BLUE NO. 1; FD&C YELLOW NO. 5

Colgate® Max Fresh® Clean Mint Fluoride Toothpaste

Drug Facts

Active ingredient

Sodium fluoride 0.24% (0.15% w/v fluoride ion)

Purpose

Anticavity

Use

helps protect against cavities

Warnings

Keep out of reach of children under 6 years of age.

WHEN USING

If more than used for brushing is accidentally swallowed, get medical help or contact a Poison Control Center right away.

Directions

adults and children 2 years of age and older | brush teeth thoroughly, preferably after each meal or at least twice a day, or as directed by a dentist or physician
children 2 to 6 years | use only a pea sized amount and supervise child's brushing and rinsing (to minimize swallowing)
children under 2 years | ask a dentist or physician

Inactive ingredients

sorbitol, water, hydrated silica, PEG-12, sodium lauryl sulfate, flavor, cellulose gum, tetrasodium pyrophosphate, cocamidopropyl betaine, sodium saccharin, methylcellulose, FD&C blue no. 1, FD&C yellow no. 5

Questions?

1-800-468-6502

Dist. by:
COLGATE-PALMOLIVE COMPANY
New York, NY 10022

PRINCIPAL DISPLAY PANEL - 170 g Tube Carton

Colgate®

Anticavity

Fluoride Toothpaste

Bursting with Freshness That Lasts for Hours!

WITH WHITENING

maxFresh®

WITH
MINI BREATH STRIPS

CLEAN MINT

NET WT 6.0 OZ (170 g)